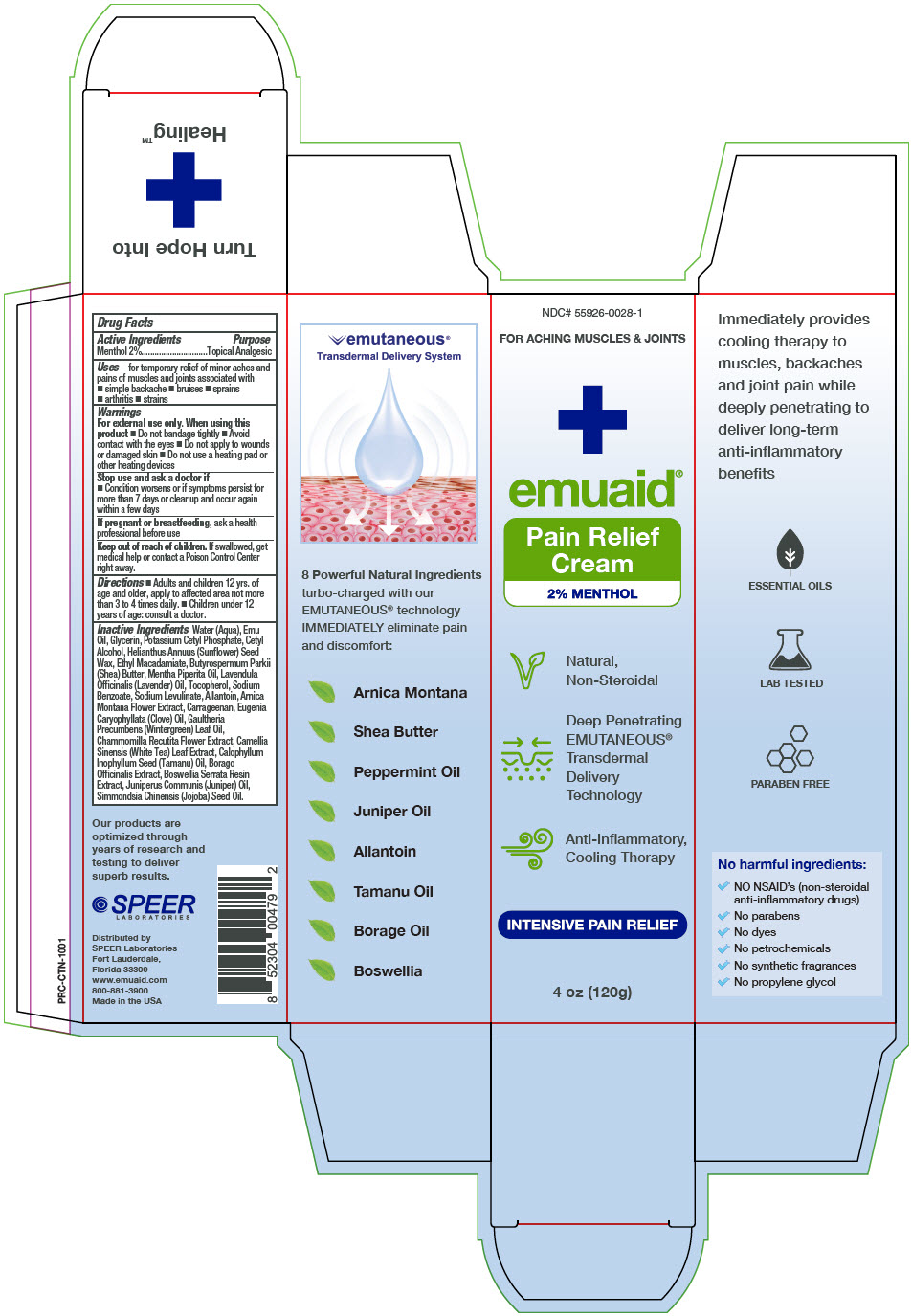 DRUG LABEL: EMUAID Pain Relief
NDC: 55926-0028 | Form: CREAM
Manufacturer: Speer Laboratories LLC
Category: otc | Type: HUMAN OTC DRUG LABEL
Date: 20250225

ACTIVE INGREDIENTS: MENTHOL, UNSPECIFIED FORM 2.4 g/120 g
INACTIVE INGREDIENTS: WATER; EMU OIL; GLYCERIN; POTASSIUM CETYL PHOSPHATE; CETYL ALCOHOL; HELIANTHUS ANNUUS SEED WAX; ETHYL MACADAMIATE; SHEA BUTTER; PEPPERMINT OIL; LAVENDER OIL; TOCOPHEROL; SODIUM BENZOATE; SODIUM LEVULINATE; ALLANTOIN; ARNICA MONTANA FLOWER; CARRAGEENAN; CLOVE OIL; METHYL SALICYLATE; CHAMOMILE; GREEN TEA LEAF; TAMANU OIL; BORAGE; INDIAN FRANKINCENSE; JUNIPER BERRY OIL; JOJOBA OIL

EMUAID® Pain Relief Cream

Drug Facts

Active Ingredients

Menthol 2%

Purpose

Topical Analgesic

Uses

for temporary relief of minor aches and pains of muscles and joints associated with

- simple backache
- bruises
- sprains
- arthritis
- strains

Warnings

For external use only. When using this product

- Do not bandage tightly
- Avoid contact with the eyes
- Do not apply to wounds or damaged skin
- Do not use a heating pad or other heating devices

Stop use and ask a doctor if

- Condition worsens or if symptoms persist for more than 7 days or clear up and occur again within a few days

PREGNANCY OR BREAST FEEDING

If pregnant or breastfeeding, ask a health professional before use

Keep out of reach of children. If swallowed, get medical help or contact a Poison Control Center right away.

Directions

- Adults and children 12 yrs. of age and older, apply to affected area not more than 3 to 4 times daily.
- Children under 12 years of age: consult a doctor.

Inactive Ingredients

Water (Aqua), Emu Oil, Glycerin, Potassium Cetyl Phosphate, Cetyl Alcohol, Helianthus Annuus (Sunflower) Seed Wax, Ethyl Macadamiate, Butyrospermum Parkii (Shea) Butter, Mentha Piperita Oil, Lavendula Officinalis (Lavender) Oil, Tocopherol, Sodium Benzoate, Sodium Levulinate, Allantoin, Arnica Montana Flower Extract, Carrageenan, Eugenia Caryophyllata (Clove) Oil, Gaultheria Precumbens (Wintergreen) Leaf Oil, Chammomilla Recutita Flower Extract, Camellia Sinensis (White Tea) Leaf Extract, Calophyllum Inophyllum Seed (Tamanu) Oil, Borago Officinalis Extract, Boswellia Serrata Resin Extract, Juniperus Communis (Juniper) Oil, Simmondsia Chinensis (Jojoba) Seed Oil.

Distributed by
SPEER Laboratories
Fort Lauderdale,
Florida 33309

PRINCIPAL DISPLAY PANEL - 120 g Tube Box

NDC# 55926-0028-1

FOR ACHING MUSCLES & JOINTS

emuaid®

Pain Relief
Cream
2% MENTHOL

Natural,
Non-Steroidal

Deep Penetrating
EMUTANEOUS®
Transdermal
Delivery
Technology

Anti-Inflammatory,
Cooling Therapy

INTENSIVE PAIN RELIEF

4 oz (120g)